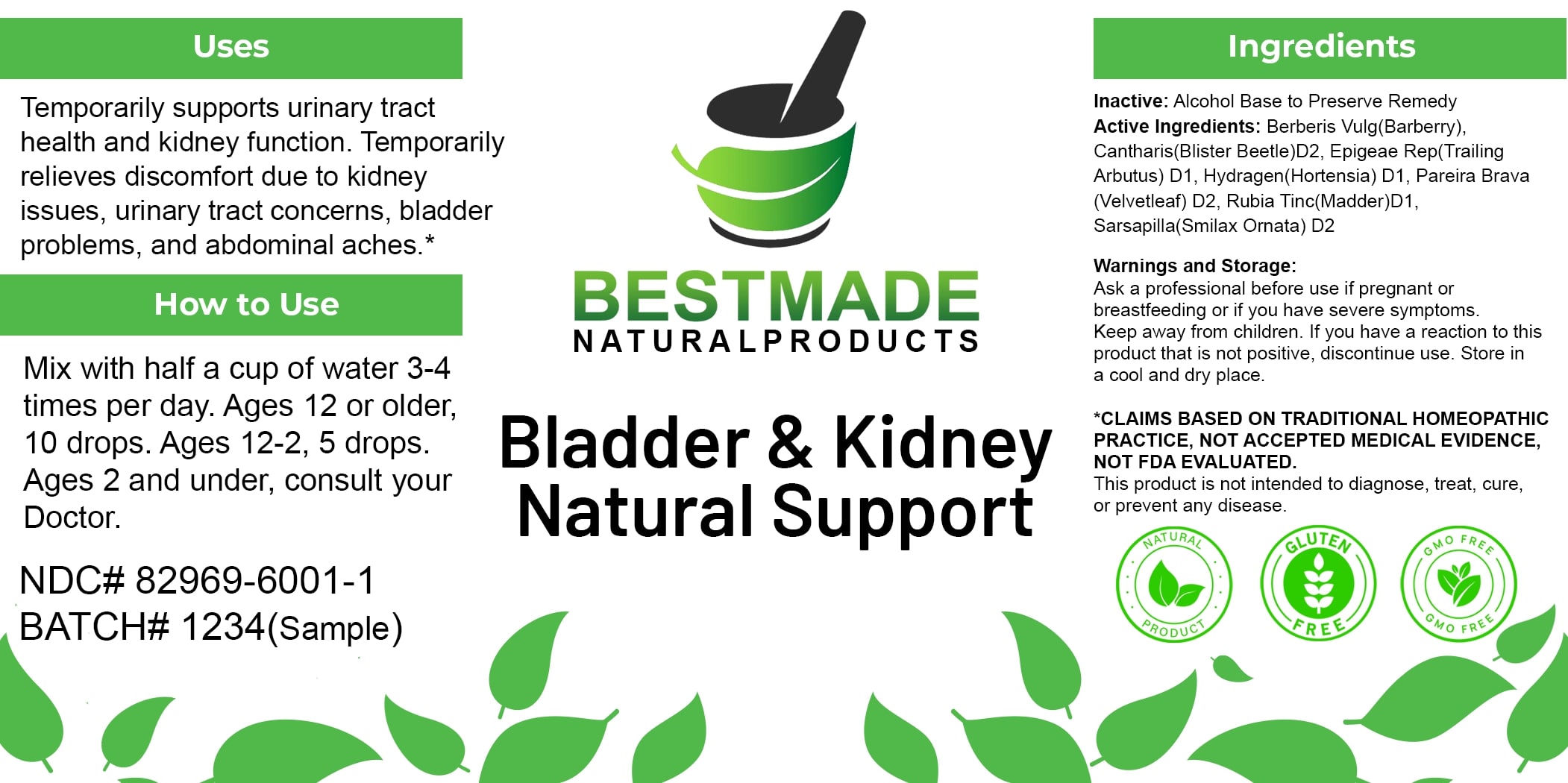 DRUG LABEL: Bestmade Natural Products Bladder and Kidney Natural Support
NDC: 82969-6001 | Form: LIQUID
Manufacturer: Bestmade Natural Products
Category: homeopathic | Type: HUMAN OTC DRUG LABEL
Date: 20250307

ACTIVE INGREDIENTS: EPIGAEA REPENS 30 [hp_C]/30 [hp_C]; RUBIA TINCTORUM ROOT 30 [hp_C]/30 [hp_C]; SARSAPARILLA 30 [hp_C]/30 [hp_C]; BERBERIS VULGARIS ROOT BARK 30 [hp_C]/30 [hp_C]; HYDRANGEA ARBORESCENS ROOT 30 [hp_C]/30 [hp_C]; CHONDRODENDRON TOMENTOSUM ROOT 30 [hp_C]/30 [hp_C]; LYTTA VESICATORIA 30 [hp_C]/30 [hp_C]
INACTIVE INGREDIENTS: ALCOHOL 30 [hp_C]/30 [hp_C]

Bladder support & Kidney Cleanse

DOSAGE AND ADMINISTRATION

How to Use

Mix with half a cup of water 3-4 times per day. Ages 12 or older, 10 drops. Ages 12-2, 5 drops. Ages 2 and under, consult your Doctor.

Uses

Temporarily supports urinary tract health and kidney function. Temporarily relieves discomfort due to kidney issues, urinary tract concerns, bladder problems, and abdominal aches.*

*CLAIMS BASED ON TRADITIONAL HOMEOPATHIC PRACTICE, NOT ACCEPTED MEDICAL EVIDENCE, NOT FDA EVALUATED.

This product is not intended to diagnose, treat, cure, or prevent any disease.

Uses

Temporarily supports urinary tract health and kidney function. Temporarily relieves discomfort due to kidney issues, urinary tract concerns, bladder problems, and abdominal aches.*

*CLAIMS BASED ON TRADITIONAL HOMEOPATHIC PRACTICE, NOT ACCEPTED MEDICAL EVIDENCE, NOT FDA EVALUATED.

This product is not intended to diagnose, treat, cure, or prevent any disease.

INACTIVE INGREDIENT

Ingredients

Inactive: Alcohol Base to Preserve Remedy

ACTIVE INGREDIENT

Active Ingredients: Berberis Vulg(Barberry), Cantharis(Blister Beetle) D2, Epigeae Rep(Trailing Arbutus) D1, Hydragen(Hortensia) D1, Pareira Brava(Velvetleaf) D2, Rubia Tinc(Madder) D1, Sarsapilla(Smilax Ornata) D2

KEEP OUT OF REACH OF CHILDREN

Warnings and Storage:

Ask a professional before use if pregnant or breastfeeding or if you have severe symptoms. Keep away from children. If you have a reaction to this product that is not positive, discontinue use. Store in a cool and dry place.

Warnings and Storage:

Ask a professional before use if pregnant or breastfeeding or if you have severe symptoms. Keep away from children. If you have a reaction to this product that is not positive, discontinue use. Store in a cool and dry place.

*CLAIMS BASED ON TRADITIONAL HOMEOPATHIC PRACTICE, NOT ACCEPTED MEDICAL EVIDENCE, NOT FDA EVALUATED.

This product is not intended to diagnose, treat, cure, or prevent any disease.

Entire package label